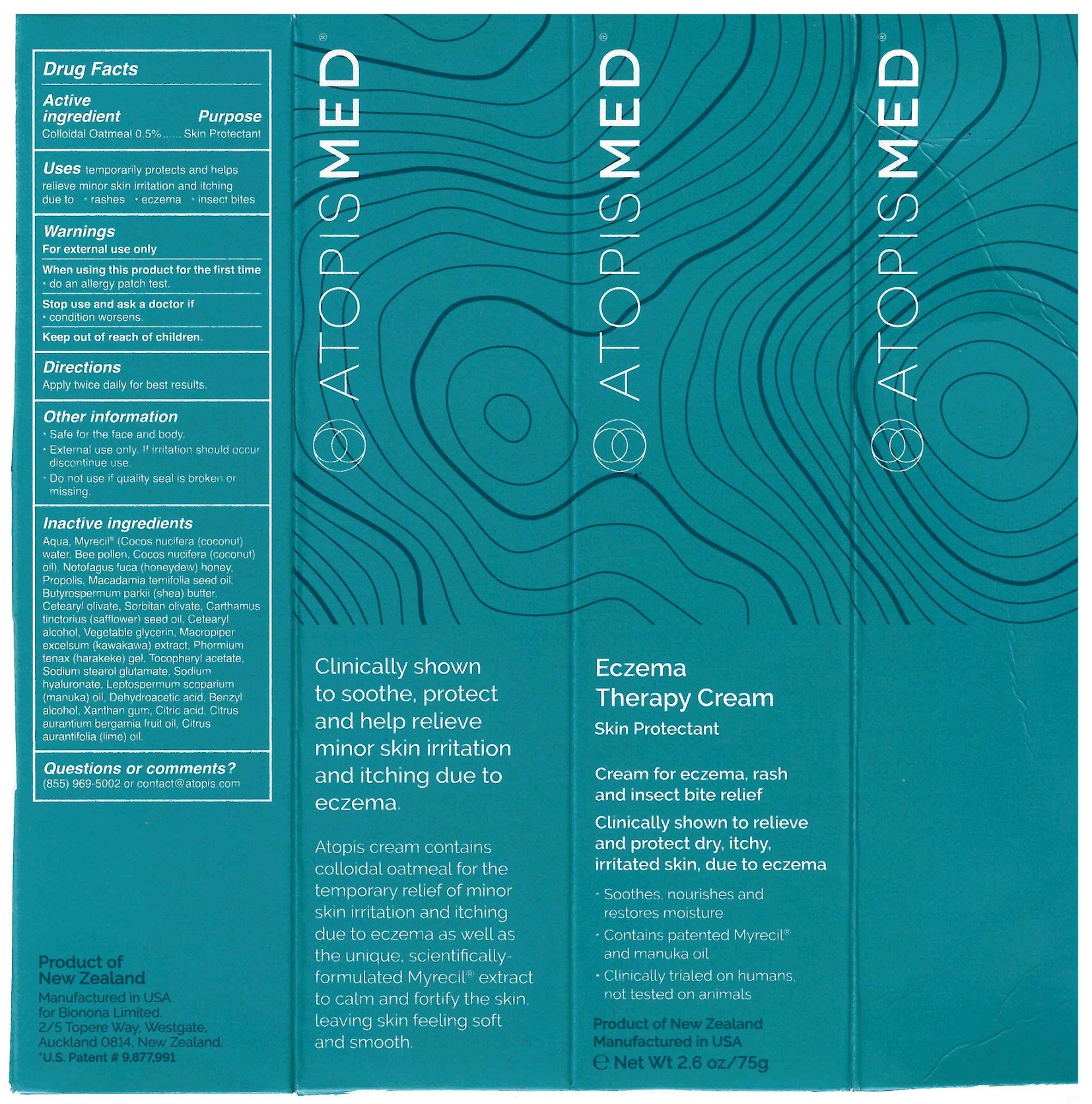 DRUG LABEL: Atopis Med
NDC: 65112-269 | Form: CREAM
Manufacturer: I Shay Cosmetics Inc
Category: otc | Type: HUMAN OTC DRUG LABEL
Date: 20211203

ACTIVE INGREDIENTS: OATMEAL 0.005 g/1 g
INACTIVE INGREDIENTS: WATER 0.676 g/1 g

Bionona Atopis Med

Warnings

For external use only

When using this product for the first time

-do an allergy patch test

Stop use and ask a Doctor if

-condition worsens

Keep out of reach of children

Uses

temporarily protects and helps relieve minor skin irritation and itching due to rashes, eczema, insect bites

Indications & Usage Section

Uses temporarily protects and helpsrelieve minor skin irritation and itching due to rashes eczema insect bites

Directions Apply twice daily for best results

OTC Active Ingredient Section

Colloidal Oats 0.5%

Keep Out of Reach of Children

Dosage & Administration

Apply twice daily for best results.

Inactive ingredients

Water, Myrecil, Olivem 1000, Cetearyl alcohol, Endmusol 20D, Macadamia oil, Safflower oil, Shea butter, glycerin, Harakeke gel, Geogard 221, Hyaluronic acid, Lavender oil, Tocopherol acetate, Manuka oil, Manuka honey, Citric acid, Xantham gum